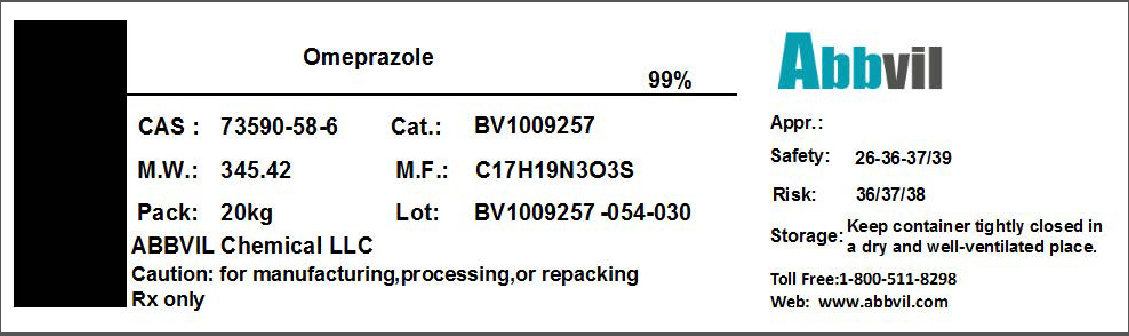 DRUG LABEL: OMEPRAZOLE
NDC: 86065-002 | Form: POWDER
Manufacturer: Abbvil Chemical LLC
Category: other | Type: BULK INGREDIENT
Date: 20160408

ACTIVE INGREDIENTS: OMEPRAZOLE 0.99 kg/1 kg

Omeprazole